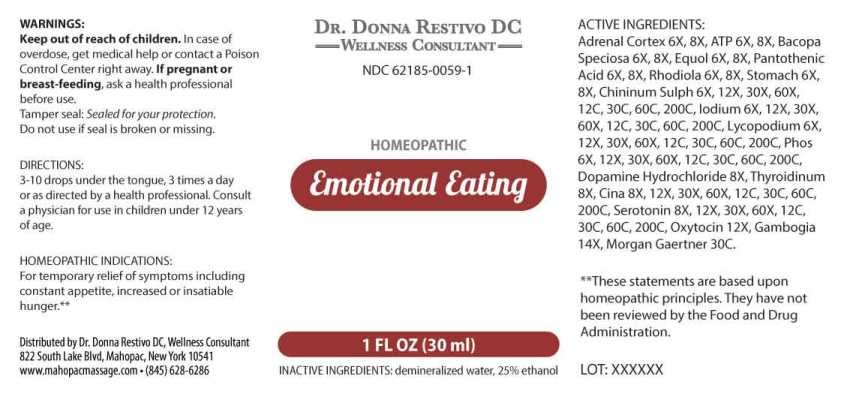 DRUG LABEL: Emotional Eating
NDC: 62185-0059 | Form: LIQUID
Manufacturer: Dr. Donna Restivo DC
Category: homeopathic | Type: HUMAN OTC DRUG LABEL
Date: 20250523

ACTIVE INGREDIENTS: ADENOSINE TRIPHOSPHATE DISODIUM 6 [hp_X]/1 mL; SUS SCROFA ADRENAL CORTEX 6 [hp_X]/1 mL; BACOPA MONNIERI WHOLE 6 [hp_X]/1 mL; EQUOL, (+/-)- 6 [hp_X]/1 mL; PANTOTHENIC ACID 6 [hp_X]/1 mL; SEDUM ROSEUM ROOT 6 [hp_X]/1 mL; SUS SCROFA STOMACH 6 [hp_X]/1 mL; QUININE SULFATE 6 [hp_X]/1 mL; IODINE 6 [hp_X]/1 mL; LYCOPODIUM CLAVATUM SPORE 6 [hp_X]/1 mL; PHOSPHORUS 6 [hp_X]/1 mL; DOPAMINE HYDROCHLORIDE 8 [hp_X]/1 mL; THYROID 6 [hp_X]/1 mL; ARTEMISIA CINA PRE-FLOWERING TOP 8 [hp_X]/1 mL; SEROTONIN HYDROCHLORIDE 8 [hp_X]/1 mL; OXYTOCIN ACETATE 12 [hp_X]/1 mL; GAMBOGE 14 [hp_X]/1 mL; SALMONELLA ENTERICA SUBSP. ENTERICA SEROVAR ENTERITIDIS 30 [hp_C]/1 mL
INACTIVE INGREDIENTS: WATER; ALCOHOL

DRUG FACTS:

ACTIVE INGREDIENTS:

Adenosinum Triphosphoricum Dinatrum 6X, 8X, Adrenal Cortex (Suis) 6X, 8X, Bacopa Speciosa 6X, 8X, Equol 6X, 8X, Pantothenic Acid 6X, 8X, Rhodiola 6X, 8X, Stomach (Suis) 6X, 8X, Chininum Sulphuricum 6X, 12X, 30X, 60X, 12C, 30C, 60C, 200C, Iodium 6X, 12X, 30X, 60X, 12C, 30C, 60C, 200C, Lycopodium Clavatum 6X, 12X, 30X, 60X, 12C, 30C, 60C, 200C, Phosphorus 6X, 12X, 30X, 60X, 12C, 30C, 60C, 200C, Dopamine Hydrochloride 8X, Thyroidinum (Suis) 8X, Cina 8X, 12X, 30X, 60X, 12C, 30C, 60C, 200C, Serotonin (Hydrochloride) 8X, 12X, 30X, 60X, 12C, 30C, 60C, 200C, Oxytocin Acetate 12X, Gambogia 14X, Morgan Gaertner 30C.

HOMEOPATHIC INDICATIONS:

For temporary relief of symptoms including constant appetite, increased or insatiable hunger.**

**These statements are based upon homeopathic principles. They have not been reviewed by the Food and Drug Administration.

WARNINGS:

Keep out of reach of children. In case of overdose, get medical help or contact a Poison Control Center right away.

If pregnant or breast-feeding, ask a health professional before use.

Tamper seal: Sealed for your protection. Do not use if seal is broken or missing.

KEEP OUT OF REACH OF CHILDREN:

In case of overdose, get medical help or contact a Poison Control Center right away.

DIRECTIONS:

3-10 drops under the tongue, 3 times a day or as directed by a health professional. Consult a physician for use in children under 12 years of age.

HOMEOPATHIC INDICATIONS:

For temporary relief of symptoms including constant appetite, increased or insatiable hunger.**

**These statements are based upon homeopathic principles. They have not been reviewed by the Food and Drug Administration.

INACTIVE INGREDIENTS:

demineralized water, 25% ethanol

QUESTIONS:

Distributed by Dr. Donna Restivo DC, Wellness Consultant

822 South Lake Blvd, Mahopac, New York 10541

www.mahopacmassage.com • (845) 628-6286

PACKAGE LABEL DISPLAY:

Dr. Donna Restivo DC

Wellness Consultant

NDC 62185-0059-1

HOMEOPATHIC

Emotional Eating

1 FL OZ (30 ml)